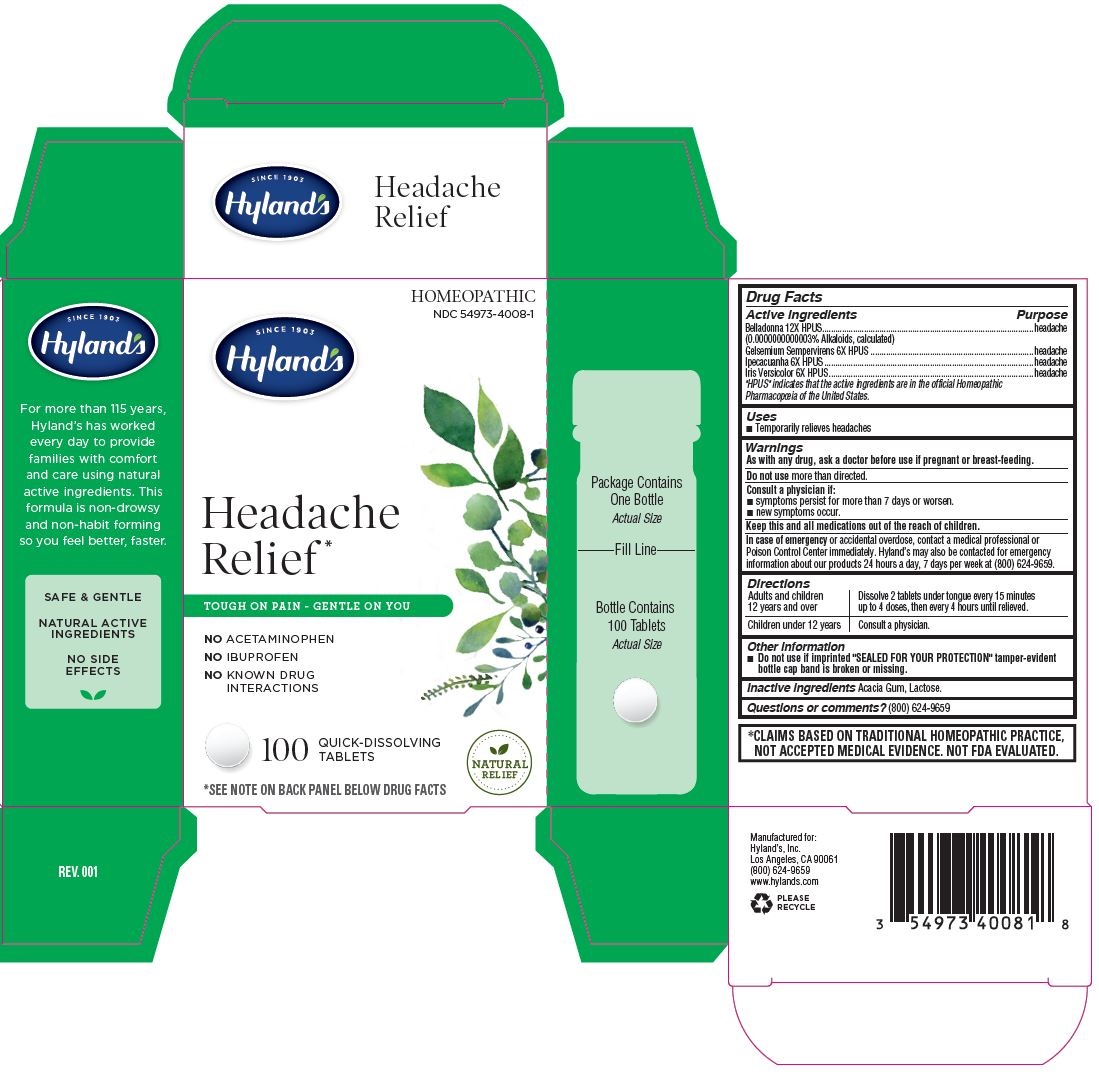 DRUG LABEL: Headache Relief
NDC: 54973-4008 | Form: TABLET
Manufacturer: Hyland's Inc.
Category: homeopathic | Type: HUMAN OTC DRUG LABEL
Date: 20221212

ACTIVE INGREDIENTS: GELSEMIUM SEMPERVIRENS ROOT 6 [hp_X]/1 1; IPECAC 6 [hp_X]/1 1; ATROPA BELLADONNA 12 [hp_X]/1 1; IRIS VERSICOLOR ROOT 6 [hp_X]/1 1
INACTIVE INGREDIENTS: ACACIA; LACTOSE MONOHYDRATE

Hyland's Headache Relief

PURPOSE

Headache Relief

Drug Facts

Active ingredients

Active ingredients | Purpose
Belladonna 12X HPUS; (0.0000000000003% Alkaloids, calculated) | headache
Gelsemium Sempervirens 6X HPUS | headache
Ipecacuanha 6X HPUS | headache
Iris Versicolor 6X HPUS | headache

"HPUS" indicates that the active ingredients are in the official Homeopathic

Pharmacopoeia of the United States.

Uses

■ Temporarily relieves headaches

Warnings

PREGNANCY OR BREAST FEEDING

As with any drug, ask a doctor before use if pregnant or breast-feeding.

Do not use more than directed.

ASK DOCTOR

Consult a physician if:

■ symptoms persist for more than 7 days or worsen.

■ new symptoms occur.

KEEP OUT OF REACH OF CHILDREN

Keep this and all medications out of the reach of children.

OVERDOSAGE

In case of emergency or accidental overdose, contact a medical professional or Poison Control Center immediately. Hyland’s may also be contacted for emergency information about our products 24 hours a day, 7 days per week at (800) 624-9659.

Directions

Adults and children; 12 years and over | Dissolve 2 tablets under tongue every 15 minutes; up to 4 doses, then every 4 hours until relieved.
Children under 12 years | Consult a physician.

Other information

■ Do not use if imprinted "SEALED FOR YOUR PROTECTION" tamper-evident bottle cap band is broken or missing.

Inactive ingredients

Acacia Gum, Lactose.

Questions or comments?

(800) 624-9659

*CLAIMS BASED ON TRADITIONAL HOMEOPATHIC PRACTICE, NOT ACCEPTED MEDICAL EVIDENCE. NOT FDA EVALUATED.

Principal Display Panel

HOMEOPATHIC

NDC 54973-4008-1

SINCE 1903

Hyland's

Headache

Relief *

TOUGH ON PAIN - GENTLE ON YOU

NO ACETAMINOPHEN

NO IBUPROFEN

NO KNOWN DRUG

INTERACTIONS

100 QUICK-DISSOLVING

TABLETS

NATURAL

RELIEF

*SEE NOTE ON BACK PANEL BELOW DRUG FACTS